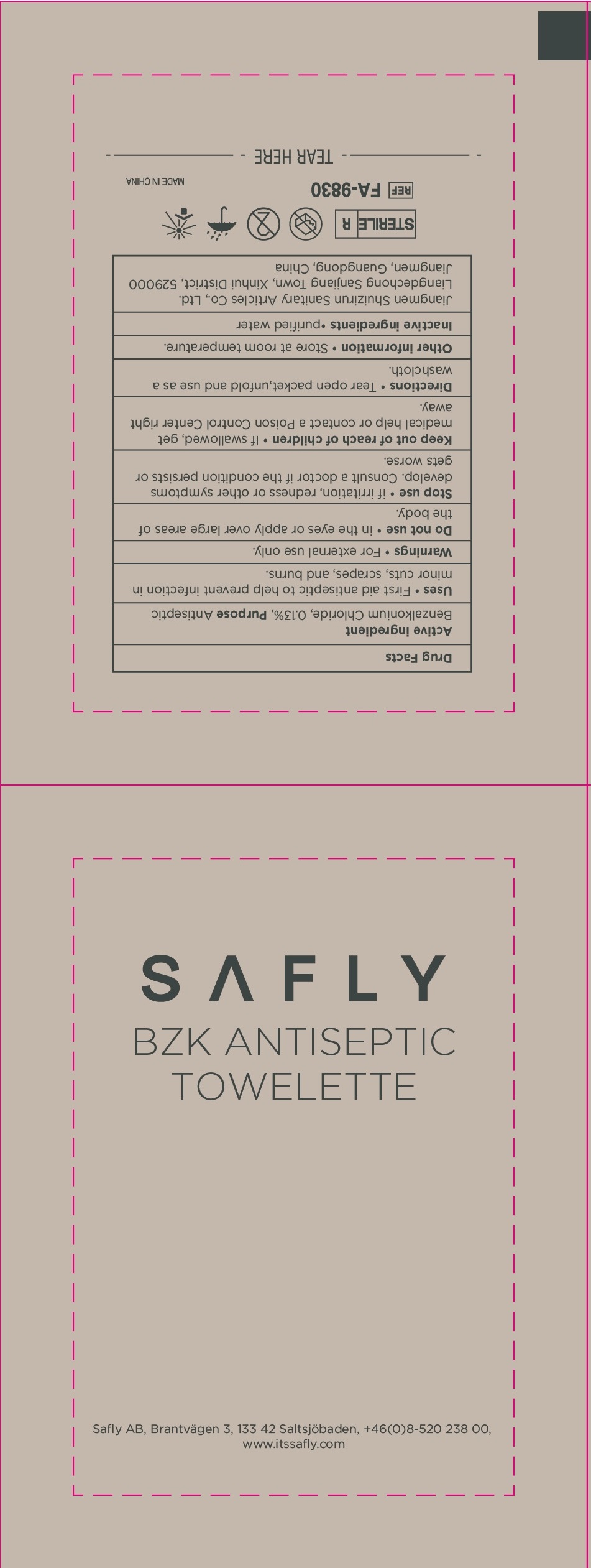 DRUG LABEL: Safly BZK Antiseptic Towelette
NDC: 71734-116 | Form: SWAB
Manufacturer: JIANGMEN SHUIZIRUN SANITARY ARTICLES CO., LTD.
Category: otc | Type: HUMAN OTC DRUG LABEL
Date: 20240515

ACTIVE INGREDIENTS: BENZALKONIUM CHLORIDE 0.13 g/100 g
INACTIVE INGREDIENTS: WATER

safly bzk antiseptic towelette

DRUG FACTS

Active Ingredient

Benzalkonium Chloride .......... 0.13 %

Purpose

Antiseptic

Uses:

First aid antiseptic to help prevent infection in minor cuts, scrapes and burns.

Warnings

For external use only.

Stop use if irritation, redness or other symptoms develop. Consult a doctor if the condition persists or gets worse.

Keep out of reach of children. If swallowed, get medical help or contact a Poison Control Center right away.

Directions

Tear open packet,unfold and use as a washcloth.

Other Information:

Store at room temperature.

Inactive Ingredients:

Purified Water